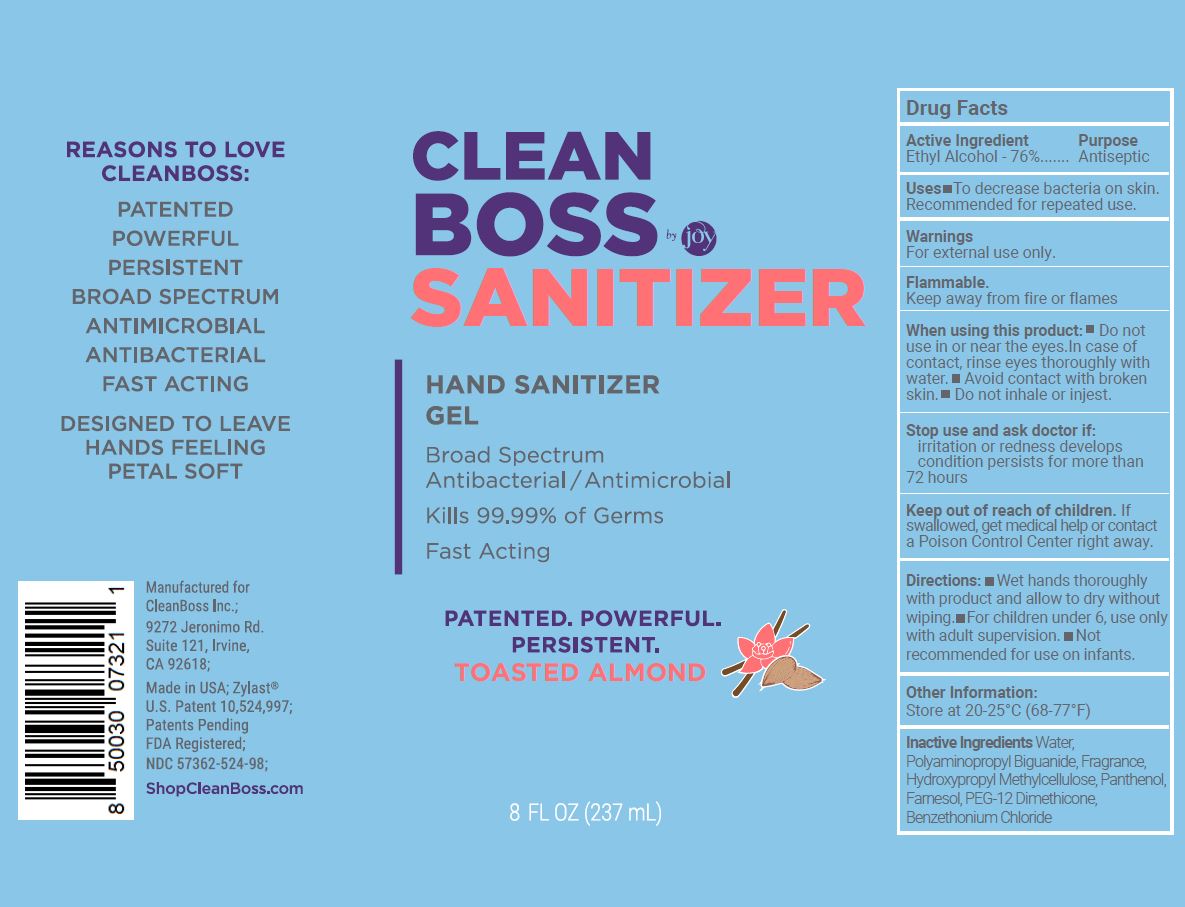 DRUG LABEL: CleanBoss Hand Sanitizing Gel
NDC: 57362-524 | Form: GEL
Manufacturer: Innovative Biodefense
Category: otc | Type: HUMAN OTC DRUG LABEL
Date: 20251002

ACTIVE INGREDIENTS: ALCOHOL 76 mL/100 mL
INACTIVE INGREDIENTS: WATER

CleanBoss
Toasted Almond
Hand Sanitizer Gel

ACTIVE INGREDIENT

Ethyl Alcohol - 76%

PURPOSE

Antiseptic

INDICATIONS AND USAGE

- To decrease bacteria on skin.
- Recommended for repeated use.

WARNINGS

For external use only.

Flammable

Keep away from fire or flames.

- Do not use in or near the eyes. In case of contact, rinse eyes thoroughly with water.
- Avoid contact with broken skin.
- Do not inhale or ingest.

STOP USE

- Irritation or redness develops.
- Condition persists for more than 72 hours.

KEEP OUT OF REACH OF CHILDREN

If swallowed, get medical help or contact a Poison Center right away.

DOSAGE AND ADMINISTRATION

- Wet hands thoroughly with product and allow to dry without wiping.
- For children under 6, use only with adult supervision.
- Not recommended for use on infants.

OTHER SAFETY INFORMATION

Store at 20-25ºC (68-77ºF)

INACTIVE INGREDIENT

Benzethonium Chloride, Dimethicone, Farnesol, Fragrance, Hydroxypropyl Methylcellulose, Panthenol, PEG-12, Polyaminopropyl Biguanide, Water